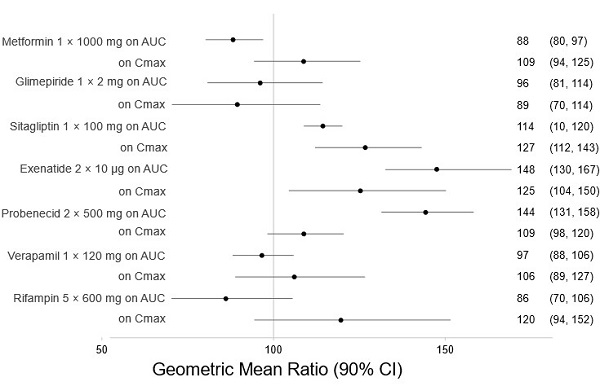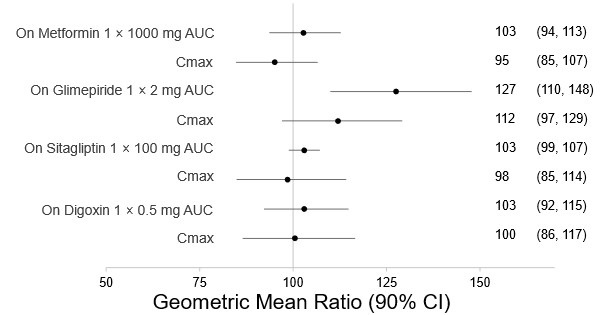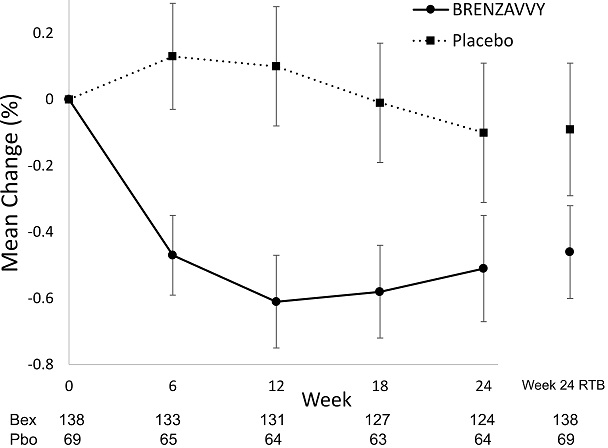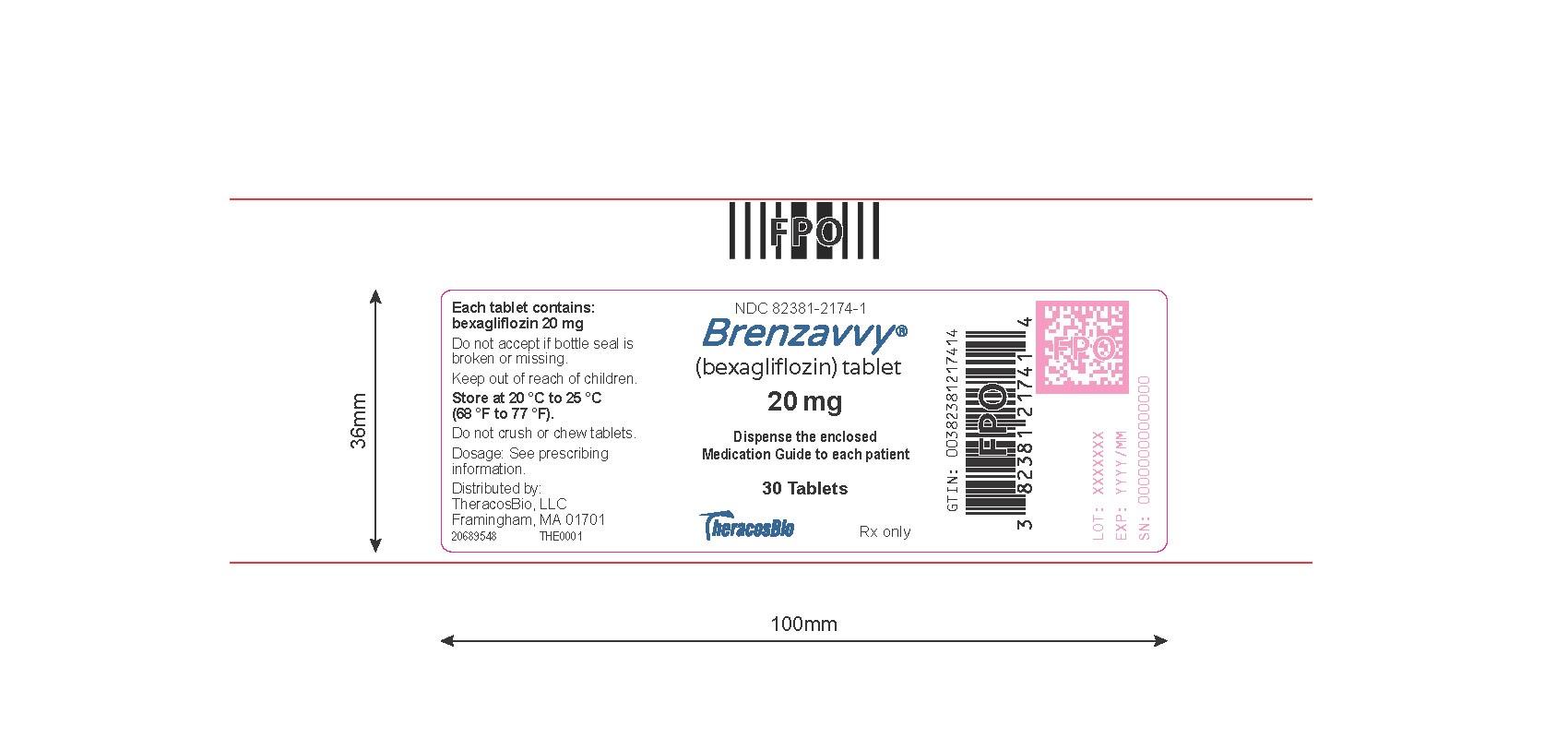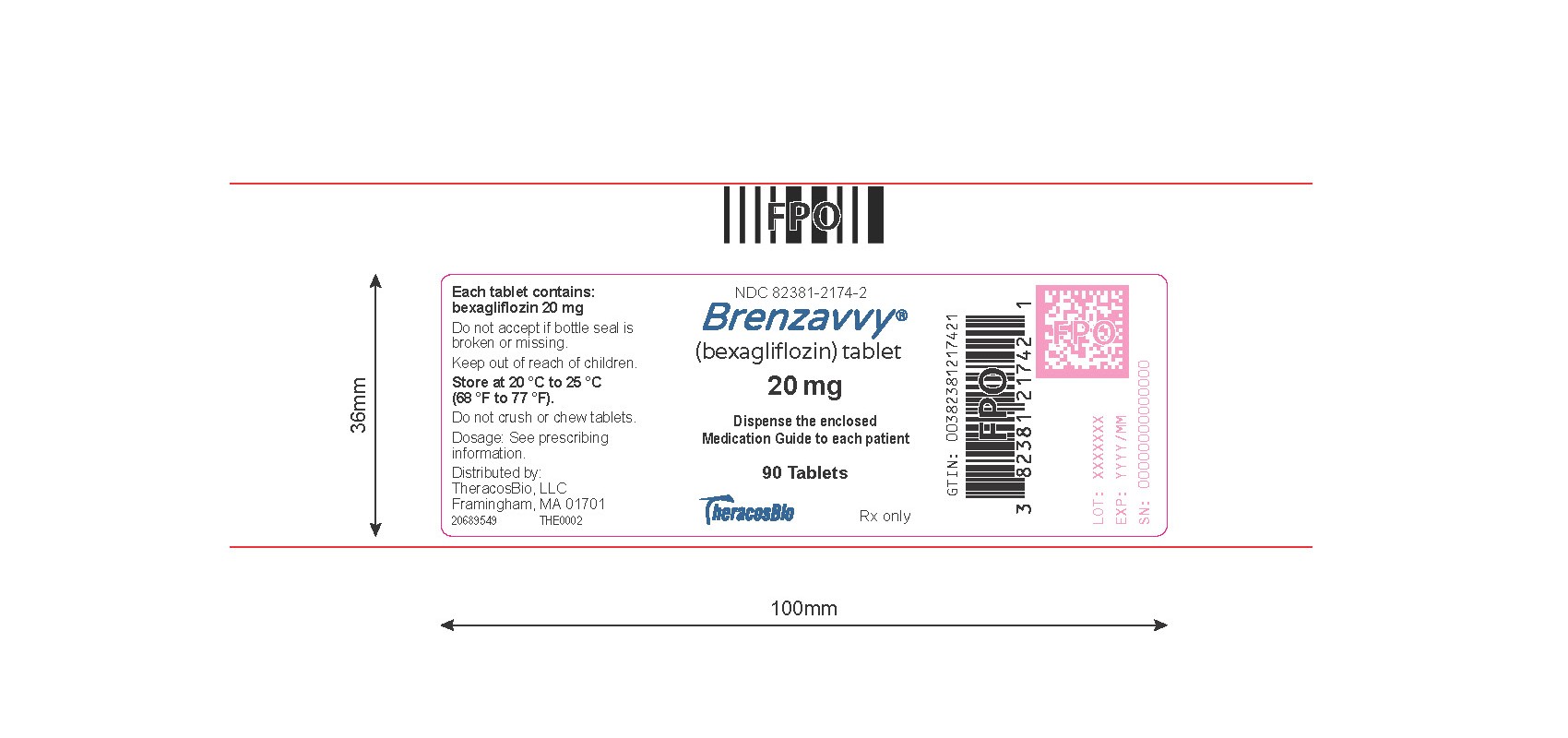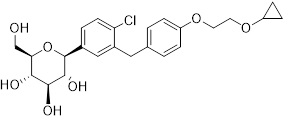 DRUG LABEL: BRENZAVVY
NDC: 82381-2174 | Form: TABLET
Manufacturer: TheracosBio, LLC
Category: prescription | Type: Human Prescription Drug Label
Date: 20251111

ACTIVE INGREDIENTS: BEXAGLIFLOZIN 20 mg/1 1
INACTIVE INGREDIENTS: FD&C BLUE NO. 1; GLYCERYL DIBEHENATE; INDIGOTINDISULFONATE SODIUM; LACTOSE MONOHYDRATE; MAGNESIUM STEARATE; MICROCRYSTALLINE CELLULOSE; SILICON DIOXIDE; POLYETHYLENE GLYCOL 3350; POLYETHYLENE GLYCOL, UNSPECIFIED; POLOXAMER 188; POLYVINYL ALCOHOL, UNSPECIFIED; TITANIUM DIOXIDE; TALC

HIGHLIGHTS OF PRESCRIBING INFORMATION

These highlights do not include all the information needed to use BRENZAVVY safely and effectively. See full prescribing information for BRENZAVVY.
BRENZAVVY (bexagliflozin) tablets, for oral use
Initial U.S. Approval: 2023

RECENT MAJOR CHANGES

Warnings and Precautions (5.4) 11/2025

1 INDICATIONS AND USAGE

BRENZAVVY is a sodium-glucose co-transporter 2 (SGLT2) inhibitor indicated as an adjunct to diet and exercise to improve glycemic control in adults with type 2 diabetes mellitus. (1)
Limitation of Use: Not recommended for use to improve glycemic control in patients with type 1 diabetes mellitus. (1)

2 DOSAGE AND ADMINISTRATION

• Recommended dose: 20 mg once daily, taken in the morning, with or without food. Do not crush or chew the tablet. (2.2)
• Assess renal function before initiating BRENZAVVY and as clinically indicated. Correct volume depletion before initiating (2.1)
• Not recommended if eGFR less than 30 mL/min/1.73 m^2. (2.1)

• Withhold BRENZAVVY for at least 3 days, if possible, prior to major surgery or procedures associated with prolonged fasting (2.3).

3 DOSAGE FORMS AND STRENGTHS

Tablets: 20 mg

4 CONTRAINDICATIONS

• Hypersensitivity to bexagliflozin or any excipient in BRENZAVVY

5 WARNINGS AND PRECAUTIONS

- Diabetic Ketoacidosis in Patients with Type 1 Diabetes Mellitus and Other Ketoacidosis: Consider ketone monitoring in patients at risk for ketoacidosis, as indicated. Assess for ketoacidosis regardless of presenting blood glucose levels and discontinue BRENZAVVY if ketoacidosis is suspected. Monitor patients for resolution of ketoacidosis before restarting. (5.1)
- Lower limb amputation: Consider factors that may increase the risk for amputations before initiating BRENZAVVY. Monitor patients for signs and symptoms of infection, or ulcers of the lower limbs, and discontinue if these occur (5.2).

- Volume depletion: May result in acute kidney injury. Before initiating BRENZAVVY, assess and correct volume status in patients with impaired renal function or low systolic blood pressure, elderly patients or patients on diuretics. Monitor for signs and symptoms during therapy (5.3)
- Genitourinary Infections, including Urosepsis, Pyelonephritis:, Necrotizing Fasciitis of the Perineum (Fournier’s Gangrene), and Genital Mycotic Infections: Monitor patients for signs and symptoms of genitourinary infections and treat promptly, if indicated. Immediately evaluate patients presenting with pain or tenderness, erythema, or swelling in the genital or perineal area, along with fever or malaise, for necrotizing fasciitis and if suspected, discontinue BRENZAVVY, and promptly institute appropriate medical and/or surgical (intervention. (5.4)
- Hypoglycemia: Consider a lower dose of insulin or insulin secretagogue to reduce risk of hypoglycemia when used in combination with BRENZAVVY (5.5)

6 ADVERSE REACTIONS

Most common adverse reactions (incidence > 5%) are female genital mycotic infections, urinary tract infection and increased urination (6.1)

To report SUSPECTED ADVERSE REACTIONS, contact TheracosBio at 1-855-BRENZAVVY (1-855-273-6928) or FDA at 1-800-FDA-1088 or www.fda.gov/medwatch.

8 USE IN SPECIFIC POPULATIONS

- Pregnancy: Advise females of the potential risk to a fetus especially during the second and third trimesters. BRENZAVVY is not recommended during the second and third trimesters of pregnancy (8.1)
- Lactation: Not recommended when breastfeeding. (8.2)
- Geriatric patients: Higher incidence of adverse reactions related to volume depletion. (5.3, 8.5)
- Renal Impairment: Higher incidence of adverse reactions related to reduced renal function (5.3, 8.6)
- Hepatic Impairment: Not recommended for patients with severe hepatic impairment (8.7)

FULL PRESCRIBING INFORMATION

1 INDICATIONS AND USAGE

BRENZAVVY is indicated as an adjunct to diet and exercise to improve glycemic control in adults with type 2 diabetes mellitus.

Limitations of Use
BRENZAVVY is not recommended for use to improve glycemic control in patients with type 1 diabetes mellitus. [see Warnings and Precautions (5.1)].

2 DOSAGE AND ADMINISTRATION

2.1 Testing Prior to Initiation and During Treatment with BRENZAVVY

• Assess renal function prior to initiation of BRENZAVVY and periodically thereafter as clinically indicated [see Warnings and Precautions (5.3)]. BRENZAVVY is not recommended in patients with an eGFR less than 30 mL/min/1.73 m^2

• Assess volume status. In patients with volume depletion, correct this condition before initiating BRENZAVVY [see Warnings and Precautions (5.3), Use in Specific Populations (8.5, 8.6)].

2.2 Recommended Dosage

• The recommended dosage of BRENZAVVY is 20 mg orally taken once daily in the morning, with or without food [see Clinical Pharmacology (12.3)].
• Do not crush or chew the tablet.
• If a dose is missed, take the missed dose as soon as possible. Do not double the next dose.

2.3 Temporary Interruption for Surgery

• Withhold BRENZAVVY for at least 3 days, if possible, prior to major surgery or procedures associated with prolonged fasting. Resume BRENZAVVY when the patient is clinically stable and has resumed oral intake [see Warnings and Precautions (5.1) and Clinical Pharmacology (12.2)].

3 DOSAGE FORMS AND STRENGTHS

Tablets: 20 mg, blue, caplet-shaped, biconvex, bevel-edged, debossed with “2” and inverted “2” on one side.

4 CONTRAINDICATIONS

BRENZAVVY is contraindicated in patients:

- With hypersensitivity to bexagliflozin or any excipient in BRENZAVVY. Anaphylaxis and angioedema have been reported with sodium-glucose co-transporter 2 (SGLT2) inhibitors.

5 WARNINGS AND PRECAUTIONS

5.1 Diabetic Ketoacidosis in Patients with Type 1 Diabetes Mellitus and Other Ketoacidosis

In patients with type 1 diabetes mellitus, BRENZAVVY significantly increases the risk of diabetic ketoacidosis, a life-threatening event, beyond background rate. In placebo-controlled trials of patients with type 1 diabetes mellitus, the risk of ketoacidosis was markedly increased in patients who received sodium glucose transporter 2 (SGLT2) inhibitors compared to patients who received placebo. BRENZAVVY is not indicated for glycemic control in patients with type 1 diabetes mellitus.
Type 2 diabetes mellitus and pancreatic disorders (e.g., history of pancreatitis or pancreatic surgery) are also risk factors for ketoacidosis. There have been postmarketing reports of fatal events of ketoacidosis in patients with type 2 diabetes mellitus using SGLT2 inhibitors.
Precipitating conditions for diabetic ketoacidosis or other ketoacidosis include under-insulinization due to insulin dose reduction or missed insulin doses, acute febrile illness, reduced caloric intake, ketogenic diet, surgery, volume depletion, and alcohol abuse.
Signs and symptoms are consistent with dehydration and severe metabolic acidosis and include nausea, vomiting, abdominal pain, generalized malaise, and shortness of breath. Blood glucose levels at presentation may be below those typically expected for diabetic ketoacidosis (e.g., less than 250 mg/dL). Ketoacidosis and glucosuria may persist longer than typically expected. Urinary glucose excretion persists for 3 days after discontinuing BRENZAVVY [see Clinical Pharmacology (12.2)]; however, there have been postmarketing reports of ketoacidosis and/or glucosuria lasting greater than 6 days and some up to 2 weeks after discontinuation of SGLT2 inhibitors.
Consider ketone monitoring in patients at risk for ketoacidosis if indicated by the clinical situation. Assess for ketoacidosis regardless of presenting blood glucose levels in patients who present with signs and symptoms consistent with severe metabolic acidosis. If ketoacidosis is suspected, discontinue BRENZAVVY, promptly evaluate, and treat ketoacidosis, if confirmed. Monitor patients for resolution of ketoacidosis before restarting BRENZAVVY.
Withhold BRENZAVVY, if possible, in temporary clinical situations that could predispose patients to ketoacidosis. Resume BRENZAVVY when the patient is clinically stable and has resumed oral intake [see Dosage and Administration (2.3)].
Educate all patients on the signs and symptoms of ketoacidosis and instruct patients to discontinue BRENZAVVY and seek medical attention immediately if signs and symptoms occur.

5.2 Lower Limb Amputation

An increased incidence of lower limb amputations occurred in BRENZAVVY-treated patients compared to placebo-treated patients (8.3 versus 5.1 events per 1,000 patient-years) in a randomized, placebo-controlled trial evaluating patients with type 2 diabetes who had either established cardiovascular disease (CVD) or were at risk for CVD (Trial 6). Additional amputation data from Trial 6 are shown in Table 2 [see Adverse Reactions (6.1)]. Of the 23 BRENZAVVY-treated patients who had amputations, 15 were amputations of the toe and midfoot and 8 were amputations above and below the knee. Some patients had multiple amputations.

Lower limb infections, gangrene, ischemia, and osteomyelitis were the most common precipitating medical events leading to the need for an amputation. The risk of amputation was highest in patients with a baseline history of prior amputation, peripheral vascular disease, and neuropathy.

Before initiating BRENZAVVY, consider factors in the patient history that may predispose to the need for amputations, such as a history of prior amputation, peripheral vascular disease, neuropathy and diabetic foot ulcers. Counsel patients about the importance of routine preventative foot care. Monitor patients receiving BRENZAVVY for signs and symptoms of infection (including osteomyelitis), new pain or tenderness, sores or ulcers involving the lower limbs, and discontinue BRENZAVVY if these complications occur.

5.3 Volume Depletion

BRENZAVVY can cause intravascular volume contraction which may sometimes manifest as symptomatic hypotension or acute transient changes in creatinine [see Adverse Reactions (6.1)]. There have been postmarketing reports of acute kidney injury, some requiring hospitalization and dialysis, in patients with type 2 diabetes mellitus receiving SGLT2 inhibitors. Patients with impaired renal function (eGFR less than 60 mL/min/1.73 m^2) [see Use in Specific Populations (8.6)], elderly patients, patients with low systolic blood pressure, or patients on loop diuretics may be at increased risk for volume depletion or hypotension. Before initiating BRENZAVVY in patients with one or more of these characteristics, assess volume status and renal function [see Dosage and Administration (2.1)]. In patients with volume depletion, correct this condition before initiating BRENZAVVY. Monitor for signs and symptoms of volume depletion, and renal function after initiating therapy.

5.4 Genitourinary Infections, including Urosepsis, Pyelonephritis, Necrotizing Fasciitis of the Perineum (Fournier’s Gangrene), and Genital Mycotic Infections

BRENZAVVY increases urinary glucose excretion [see Clinical Pharmacology (12.2)] and increases the risk of genitourinary infections including urinary tract infections and genital mycotic infections in both male and female patients [see Adverse Reactions (6.1)].

Serious genitourinary infections, including urosepsis, pyelonephritis, and necrotizing fasciitis of the perineum (Fournier’s gangrene, a rare life-threatening infection requiring urgent surgical intervention), have occurred in patients with and without diabetes mellitus receiving SGLT2 inhibitors [see Adverse Reactions (6.1)]. Cases have required hospitalization. In patients with Fournier’s gangrene, serious outcomes have included multiple surgeries and death.

Patients with a history of chronic or recurrent genitourinary infections are more likely to develop genitourinary infections when using BRENZAVVY. Monitor patients for signs and symptoms of genitourinary infections and treat promptly, if indicated.

Immediately evaluate patients presenting with pain or tenderness, erythema, or swelling in the genial or perineal area, along with fever or malaise, for necrotizing fasciitis. If suspected, discontinue BRENZAVVY and promptly institute appropriate medical and /or surgical intervention.

5.5 Hypoglycemia with Concomitant Use with Insulin and Insulin Secretagogues

Insulin and insulin secretagogues (e.g., sulfonylureas) are known to cause hypoglycemia. BRENZAVVY may increase the risk of hypoglycemia when used in combination with insulin and/or an insulin secretagogue [see Adverse Reactions (6.1)]. A lower dose of insulin or insulin secretagogue may be required to minimize the risk of hypoglycemia when used in combination with BRENZAVVY.

6 ADVERSE REACTIONS

The following important adverse reactions are described below and elsewhere in the labeling:

- Diabetic Ketoacidosis in Patients with Type 1 Diabetes Mellitus and Other Ketoacidosis [see Warnings and Precautions (5.1)]
- Lower Limb Amputation [see Warnings and Precautions (5.2)]
- Volume Depletion [see Warnings and Precautions (5.3)]
- Genitourinary Infections, including Urosepsis, Pyelonephritis, Necrotizing Fasciitis of the Perineum (Fournier’s Gangrene), and Genital Mycotic Infections [see Warnings and Precautions (5.4)]
- Hypoglycemia with Concomitant Use with Insulin and Insulin Secretagogues [see Warnings and Precautions (5.5)]

6.1 Clinical Trials Experience

Because clinical trials are conducted under widely varying conditions, adverse reaction rates observed in the clinical trials of a drug cannot be directly compared to rates in the clinical trials of another drug and may not reflect the rates observed in practice.

Pool of Placebo-Controlled Trials Evaluating BRENZAVVY 20 mg
The data in Table 1 are derived from three trials in adults with type 2 diabetes mellitus: two 24-week placebo-controlled trials (one as monotherapy and another as add-on to metformin therapy; Trials 1 and 2, respectively) [see Clinical Studies (14.2, 14.3)] and a 12-week, placebo-controlled, dose-ranging, monotherapy trial (only the data from the 20 mg dosage of BRENZAVVY per day were included in this pool). In these pooled trials, patients received placebo (N = 300) or BRENZAVVY 20 mg (N = 372), once daily. The mean age of the population was 56 years and 5% of the patients were older than 75 years of age. Fifty-seven percent (57%) were male and 45% were White, 38% Asian, 15% Black and 2% other races. At baseline, the mean duration of type 2 diabetes mellitus was 7.7 years and the mean hemoglobin A1c (HbA1c) was 8.2%. Established microvascular complications of type 2 diabetes mellitus at baseline included diabetic nephropathy (0.8%), retinopathy (24%), and peripheral neuropathy (33%). Baseline renal function was eGFR ≥ 60 mL/min/1.73 m^2 in 98% of patients and eGFR 45 to < 60 mL/min/1.73 m^2 in 2% of patients (mean eGFR 92 mL/min/1.73 m^2).

Table 1 shows common adverse reactions associated with the use of BRENZAVVY in these trials. These adverse reactions occurred more commonly in BRENZAVVY-treated patients than placebo-treated patients, and occurred in at least 2% of BRENZAVVY-treated patients.

Table 1. Adverse Reactions in Adults with Type 2 Diabetes Mellitus - Monotherapy or in Combination with Metformin*

 | Percentage of Patients
 | Placebo N = 300 | BRENZAVVY N = 372
Increased urination a | 3 | 7
Urinary tract infection b | 4 | 6
Female genital mycotic infections c | 0 | 6
Thirst d | 2 | 3
Vaginal pruritus e | 0 | 3
Male genital mycotic infection f | 1 | 2
Hypoglycemia | 1 | 2

* The three placebo-controlled trials included two monotherapy trials and one add-on combination trial with metformin in adults with type 2 diabetes mellitus (Trials 1, 2, and a 12-week dose ranging trial). Adverse reactions were those that occurred more commonly in BRENZAVVY-treated patients than placebo-treated patients and occurred in at least 2% of BRENZAVVY-treated patients.

a Includes: polyuria, pollakiuria, micturition urgency, nocturia.
b Includes: dysuria, urinary tract infection, nitrite urine present, streptococcal urinary tract infection, cystitis.
c Includes: vulvovaginal mycotic infection, vaginal infection, genital infection fungal, vulvovaginal candidiasis. Percentages calculated with the number of female patients in each group as denominator: placebo (N = 130), BRENZAVVY (N = 156).
d Includes: thirst, polydipsia.
e Includes: pruritus genital, vulvovaginal pruritus. Percentages calculated with the number of females in each group as denominator: placebo (N = 130), BRENZAVVY (N = 156).
f Includes: balanoposthitis, genital infection fungal, tinea cruris. Percentages calculated with the number of males in each group as denominator: placebo (N = 170), BRENZAVVY (N = 216).

Clinical Trial in Patients with Increased Risk for Major Adverse Cardiovascular Events
BRENZAVVY was evaluated in a trial that enrolled adults with type 2 diabetes mellitus who had either established (CVD) or were at increased risk for CVD (Trial 6) [see Clinical Studies (14.5)]. Patients on standard of care therapy for diabetes management were randomized to receive add-on therapy with either placebo (N = 567) or BRENZAVVY 20 mg once daily (N = 1,132) for a minimum duration of 52 weeks (median duration 2.4 years). The most common adverse reactions observed in this trial were generally consistent with other trials of BRENZAVVY in adults with type 2 diabetes mellitus (see Table 1).

Other Adverse Reactions
Lower Limb Amputations
An increased incidence of non-traumatic lower limb amputations occurred in BRENZAVVY-treated patients compared to placebo-treated patients in a trial (Trial 6) that evaluated adults with type 2 diabetes mellitus who had either established CVD or were at increased risk for CVD. Patients in this trial were followed for a median duration of 2.4 years. The lower limb amputation data are shown in Table 2.

Table 2. Non-traumatic Lower Limb Amputation in Adults with Type 2 Diabetes Mellitus who had either Established Cardiovascular Disease or were at Risk for Cardiovascular Disease (Trial 6)

 | Placebo N = 567 | BRENZAVVY N = 1,132
Patients with an amputation, n (%) | 7 (1.2%) | 23 (2.0%)
Total amputations | 13 | 25
Amputation incidence rate (per 1,000 patient-years) | 5.1 | 8.3
Hazard Ratio (95% CI) | - | 1.64 (0.70, 3.82)

Note: Incidence is based on the number of patients with at least one amputation, and not the total number of amputation events. A patient’s follow-up is calculated from Day 1 to the first amputation event date. Some patients had more than one amputation.

Volume Depletion
In a trial of adults with type 2 diabetes mellitus and moderate renal impairment (Trial 5), adverse reactions related to volume depletion (e.g., dehydration, dizziness, dizziness postural, vertigo, vertigo positional, presyncope, hypotension, and orthostatic hypotension) were reported in 3.9% and 8.9% of patients treated with placebo and BRENZAVVY, respectively.
Genital Mycotic Infections
In a pool of three placebo-controlled clinical trials (12-week dose ranging trial and Trials 1 and 2), the incidence of female genital mycotic infections occurred in 0% and 5.6% of females treated with placebo and BRENZAVVY, respectively (see Table 1). In the same pool of trials, male genital mycotic infections occurred in 1.4% and 2.2% of males treated with placebo and BRENZAVVY, respectively (see Table 1). In a trial that enrolled adults with type 2 diabetes mellitus and moderate renal impairment (Trial 5), 0% and 9.2% of female patients treated with placebo and BRENZAVVY, respectively, had a genital mycotic infection.
In a trial that enrolled adults with type 2 diabetes mellitus who had either established CVD or were at increased risk for CVD (Trial 6), 2.8% and 9.0% of patients treated with placebo and BRENZAVVY, respectively, had at least one event of genital mycotic infection. In the same trial, genital mycotic infections that caused drug discontinuation were reported in 0% and 1.2% of patients treated with placebo and BRENZAVVY, respectively. Balanoposthitis was reported in 0% and 2.9% of male patients, and phimosis was reported in 0.3% and 0.5% of male patients treated with placebo and BRENZAVVY, respectively. Patients treated with BRENZAVVY with events of phimosis typically underwent circumcision.
Fractures
In a trial that enrolled adults with type 2 diabetes mellitus who had either established CVD or were at increased risk for CVD (Trial 6), the incidence rates of serious fractures, including events of hip and femur fracture, were 1.4 and 5.4 events per 1,000 patient-years of follow-up in the placebo and BRENZAVVY groups, respectively. The imbalance in serious fractures was observed within the first 6 months of therapy and remained through the end of the trial.
Hypoglycemia
The incidence of hypoglycemia by trial is shown in Table 3.

Table 3. Incidence of Overall* and Severe† Hypoglycemia in Placebo-Controlled Clinical Trials in Adults with Type 2 Diabetes Mellitus

 | Placebo | BRENZAVVY
Monotherapy (24 weeks) (Trial 1)
All subjects -Overall [N (%)] -Severe [N (%)] | N = 69 0 (0) 0 (0) | N = 138 0 (0) 0 (0)
Add-on to Metformin (24 weeks) (Trial 2)
All subjects -Overall [N (%)] -Severe [N (%)] | N = 159 0 (0) 0 (0) | N = 158 1 (0.6) 0 (0)
Add-on to Standard of Care Therapy in Patients with Moderate Renal Impairment (24 weeks) (Trial 5) β
All subjects -Overall [N (%)] -Severe [N (%)] Subjects on background insulin and/or sulfonylurea -Overall [N (%)] -Severe [N (%)] | N = 155 0 (0) 0 (0) N = 109 0 (0) 0 (0) | N = 157 2 (1.3) 1 (0.6) N = 106 2 (1.9) 1 (0.9)
Add-on to Standard of Care Therapy in Patients with Increased CV Risk (Trial 6) β
All subjects -Overall [N (%)] -Severe [N (%)] Subjects on background insulin and/or sulfonylurea -Overall [N (%)] -Severe [N (%)] | N = 567 11 (1.9) 8 (1.4) N = 454 10 (2.2) 8 (1.8) | N = 1,132 23 (2.0) 10 (0.9) N = 923 22 (2.4) 10 (1.1)

* Overall hypoglycemia: plasma or capillary glucose of less than 54 mg/dL.
† Severe hypoglycemia: patient required assistance, lost consciousness, or experienced a seizure (irrespective of blood glucose concentration).
β No restrictions were placed on background antihyperglycemic therapy (aside from treatment with another SGLT2 inhibitor) and approximately 50% of patients used insulin and/or an insulin secretagogue at baseline.
Rash and Dermatitis
In the clinical program of BRENZAVVY, one event of rash and one event of dermatitis was confirmed to be attributable to BRENZAVVY exposure by withdrawal and rechallenge. The rash and dermatitis events occurred on day 37 and day 3 of exposure to BRENZAVVY, respectively. In a trial that enrolled adults with type 2 diabetes mellitus who had either established CVD or were at increased risk for CVD (Trial 6), 3.4% and 5.4% of patients experienced at least one event of rash with placebo and BRENZAVVY, respectively.

Sepsis
BRENZAVVY was associated with an increased risk of sepsis/septic shock events, including events that may have caused or contributed to death, in a trial that enrolled adults with type 2 diabetes mellitus who had either established CVD or were at increased risk for CVD (Trial 6). Sepsis events occurred in 2 (0.4%) and 14 (1.2%) of placebo-treated patients and BRENZAVVY-treated patients in the trial, respectively. Of these, 1 sepsis event among placebo-treated patients and 3 sepsis events among BRENZAVVY-treated patients were related to urinary tract infections.

Laboratory Abnormalities
Changes in Serum Creatinine and eGFR
Initiation of BRENZAVVY causes an increase in serum creatinine and decrease in eGFR within weeks of starting therapy that stabilizes by week 6 to 12. In a trial enrolling adults with type 2 diabetes mellitus and moderate renal impairment (Trial 5), a mean change in serum creatinine of 0.0 mg/dL and a decrease in eGFR of 0.1 mL/min/1.73 m^2 was observed in the placebo group as compared to a mean increase in serum creatinine of 0.1 mg/dL and a mean decrease in eGFR of 4.6 mL/min/1.73 m^2 with BRENZAVVY, within the first 6 weeks of treatment. In a trial that enrolled adults with type 2 diabetes mellitus who had either established CVD or were at increased risk for CVD (Trial 6), an initial decrease in eGFR was seen within weeks of starting therapy (eGFR changes from baseline to week 12 of 0 and -3.1 mL/min/1.73 m^2 in the placebo and BRENZAVVY arms, respectively). Acute hemodynamic changes may play a role in the early renal function changes observed with BRENZAVVY since they are reversed after treatment discontinuation.

Increases in Low-Density Lipoprotein Cholesterol (LDL-C)
In a pool of two placebo-controlled clinical trials (Trials 1 and 2), mean LDL-C decreased by 3.8 mg/dL (3.7%) in patients treated with placebo (N = 195) and increased by 1.7 mg/dL (1.6%) in patients treated with BRENZAVVY (N = 247) at week 24. In a trial that enrolled adults with type 2 diabetes mellitus who had either established CVD or were at increased risk for CVD (Trial 6), LDL-C increased by 3 mg/dL (3.2%) and 3 mg/dL (4.1%) with placebo and BRENZAVVY treatment, respectively, at Week 24.

Increases in Hemoglobin and Hematocrit
In a pool of two placebo-controlled trials (Trials 1 and 2), mean changes from baseline to Week 24 in hemoglobin were -0.3 g/dL (-2.1%) with placebo and 0.4 g/dL (2.9%) with BRENZAVVY. In the same pool, mean changes from baseline to Week 24 in hematocrit were -0.6% with placebo and 1.3% with BRENZAVVY 20 mg. Fewer patients had > 2 g/dL increases in hemoglobin from baseline for placebo (0.5%) compared to BRENZAVVY (4.9%). Increases in hemoglobin > 3 g/dL from baseline were observed in 0% of placebo-treated patients compared to 0.7% of BRENZAVVY-treated patients.

7 DRUG INTERACTIONS

See Table 4 for clinically significant interactions with BRENZAVVY.

Table 4. Clinically Significant Interactions with BRENZAVVY

UGT Enzyme Inducers
Clinical Impact | UGT Enzyme Inducers may significantly reduce exposure to BRENZAVVY and lead to a decreased efficacy [see Clinical Pharmacology (12.3)].
Intervention | Consider adding another antihyperglycemic agent in patients who require additional glycemic control.
Concomitant Use with Insulin and Insulin Secretagogues
Clinical Impact | The risk of hypoglycemia is increased when BRENZAVVY is used in combination with insulin and/or an insulin secretagogue.
Intervention | A lower dose of insulin or insulin secretagogue may be required to minimize the risk of hypoglycemia when used in combination with BRENZAVVY.
Lithium
Clinical Impact | Concomitant use with SGLT2 inhibitors such as BRENZAVVY may decrease serum lithium concentrations.
Intervention | Monitor serum lithium concentration more frequently upon BRENZAVVY initiation and discontinuation.
Positive Urine Glucose Test
Clinical Impact | SGLT2 inhibitors increase urinary glucose excretion and will lead to positive urine glucose tests.
Intervention | Monitoring glycemic control with urine glucose tests is not recommended in patients taking SGLT2 inhibitors. Use alternative methods to monitor glycemic control.
Interference with 1,5-anhydroglucitol (1,5-AG) Assay
Clinical Impact | Measurements of 1,5-AG are unreliable in assessing glycemic control in patients taking SGLT2 inhibitors.
Intervention | Monitoring glycemic control with 1,5-AG assay is not recommended. Use alternative methods to monitor glycemic control.

8 USE IN SPECIFIC POPULATIONS

8.1 Pregnancy

Risk Summary
Based on animal data showing adverse renal effects, BRENZAVVY is not recommended during the second and third trimesters of pregnancy.

The available data on use of BRENZAVVY during pregnancy are insufficient to determine a drug-associated risk of major birth defects, miscarriage, or other adverse maternal or fetal outcomes. There are risks to the mother and fetus associated with poorly controlled diabetes in pregnancy (see Clinical Considerations).

In animal studies, adverse renal pelvic and tubule dilatations that were not fully reversible were observed in rats when bexagliflozin was administered during a period of renal development corresponding to the late second and third trimesters of human pregnancy at exposures 11 times the 20 mg clinical dose (see Data).
The estimated background risk of major birth defects is 6% to 10% in women with pre-gestational diabetes with a peri-conceptional HbA1c > 7% and has been reported to be as high as 20% to 25% in women with a peri-conceptional HbA1c > 10%. The estimated background risk of miscarriage for the indicated population is unknown. In the U.S. general population, the estimated background risk of major birth defects and miscarriage in clinically recognized pregnancies is 2% to 4% and 15% to 20%, respectively.

Clinical Considerations
Disease-Associated Maternal and/or Embryo/Fetal Risk
Hypoglycemia and hyperglycemia occur more frequently during pregnancy in patients with pre-gestational diabetes. Poorly controlled diabetes in pregnancy increases the maternal risk for diabetic ketoacidosis, preeclampsia, spontaneous abortions, preterm delivery, and delivery complications. Poorly controlled diabetes increases the fetal risk for major birth defects, stillbirth, and macrosomia related morbidity.

Data
Animal Data
Bexagliflozin administered to juvenile rats at 0.3, 3 or 30 mg/kg/day by oral gavage from postnatal days 21 to 90 caused a dose dependent increase in the incidence and severity of renal pelvic and tubular dilatation at ≥ 3 mg/kg (11 times the clinical dose of 20 mg based on AUC). These outcomes occurred with drug exposure during periods of renal development in rats equivalent to the late second and third trimester of human renal development and did not fully reverse following a 1-month recovery period.

In embryofetal development studies in rats and rabbits, bexagliflozin was administered at 7, 40, and 200 mg/kg/day (rats) and 5, 25, and 150 mg/kg/day (rabbits) during organogenesis. No adverse developmental effects were observed in rats at doses up to 200 mg/kg/day (551 times the clinical dose of 20 mg based on AUC). Reduced maternal body weight, embryo lethality, and fetal malformations were observed in rabbits at 150 mg/kg/day (368 times the clinical dose of 20 mg based on AUC).

In a prenatal and postnatal development study, bexagliflozin was administered to maternal rats by oral gavage during organogenesis and until weaning at doses of 7, 40, or 200 mg/kg/day. Maternal mortality occurred at ≥ 40 mg/kg (79 times the clinical dose of 20 mg based on AUC), primarily following parturition. Reduced gestational body weight, increased post-implantation loss, and smaller litter size were noted at 200 mg/kg (361 times the clinical dose of 20 mg based on AUC). In the offspring, lower body weight gain and decreased survival were noted at 200 mg/kg, which occurred in the presence of significant maternal toxicity.

8.2 Lactation

Risk Summary
There is no information regarding the presence of bexagliflozin in human milk, the effects on the breastfed infant or the effects on milk production. Bexagliflozin is excreted in the milk of lactating rats (see Data). When a drug is present in animal milk, it is likely that the drug will be present in human milk. Since human kidney maturation occurs in utero and during the first 2 years of life when lactational exposure may occur, there may be risk to the developing human kidney. Because of the potential for serious adverse reactions in a breastfed infant, including the potential for bexagliflozin to affect postnatal renal development, advise patients that use of BRENZAVVY is not recommended while breastfeeding.

Data
Bexagliflozin was present in rat milk at a milk:plasma ratio of approximately 2. The concentration of bexagliflozin in animal milk does not necessarily predict the concentration of bexagliflozin in human milk.

Juvenile rats directly exposed to bexagliflozin showed a risk to the developing kidney (renal pelvic and tubular dilatation) during the period of renal development in rats corresponding to the late second and third trimester of human renal development.

8.4 Pediatric Use

The safety and effectiveness of BRENZAVVY have not been established in pediatric patients.

8.5 Geriatric Use

In 9 clinical trials of BRENZAVVY, 1047 (40.6%) patients 65 years and older, and 212 (8.2%) patients 75 years and older were exposed to BRENZAVVY [see Clinical Studies (14)].

One of the 9 trials enrolled patients with type 2 diabetes mellitus who had either established CVD or were at increased risk for CVD (Trial 6), and had a total of 571 (50%) patients treated with BRENZAVVY who were 65 years and older, and 113 (10%) patients treated with BRENZAVVY who were 75 years and older [see Clinical Studies (14.5)]. No overall differences in the effectiveness of BRENZAVVY have been observed between patients 65 years of age and older and younger adult patients. Among patients aged 65 and older in this trial, volume depletion events were reported in 7.6% and 9.8% of patients in the placebo and BRENZAVVY groups, respectively [see Warnings and Precautions (5.3)].

8.6 Renal Impairment

BRENZAVVY is not recommended in patients with an eGFR less than 30 mL/min/1.73 m^2 due to the decline of the glucose lowering effect of BRENZAVVY and reduction in urine output in these patients [see Clinical Pharmacology (12.3)]. The recommended dosage for patients with an eGFR greater than or equal to 30 mL/min/1.73 m^2 is the same as the recommended dosage for patients with normal renal function [see Dosage and Administration (2.1)].

The safety and efficacy of BRENZAVVY in adults with type 2 diabetes mellitus and moderate renal impairment (eGFR between 30 and 60 mL/min/1.73 m^2) were evaluated in Trial 5 [see Clinical Studies (14.4)]. Efficacy and safety studies with BRENZAVVY did not enroll patients with an eGFR less than 30 mL/min/1.73 m^2.

BRENZAVVY-treated patients with renal impairment may be more likely to experience adverse reactions associated with BRENZAVVY treatment, including female genital mycotic infection, increased urination, and thirst, and may be at higher risk for volume depletion and acute kidney injury [see Warnings and Precautions (5.3) and Adverse Reactions (6.1)].

8.7 Hepatic Impairment

BRENZAVVY has not been studied in patients with severe hepatic impairment and is not recommended for use in this patient population. The recommended dosage for patients with mild to moderate hepatic impairment is the same as the recommended dosage for patients with normal hepatic function [see Clinical Pharmacology (12.3)].

10 OVERDOSAGE

In the event of an overdose of BRENZAVVY, consider contacting the Poison Help line (1-800-222-1222) or a medical toxicologist for additional overdosage management recommendations. Employ the usual supportive measures as dictated by the patient’s clinical status. Removal of bexagliflozin by hemodialysis has not been studied.

11 DESCRIPTION

BRENZAVVY tablets for oral use contain bexagliflozin, an SGLT2 inhibitor.
The chemical name of bexagliflozin is (2S,3R,4R,5S,6R)-2-(4-chloro-3-(4-(2-cyclopropoxyethoxy)benzyl)phenyl)-6-(hydroxymethyl)tetrahydro-2H-pyran-3,4,5-triol.
The molecular formula is C24H29ClO7 and the molecular weight is 464.94 g/mol. The structural formula is:

Bexagliflozin is a white/off-white to pale yellow powder. It is very slightly soluble in water and freely soluble in methanol, acetone, ethylene glycol, and propylene glycol. It is slightly soluble in heptane, cyclohexane, and toluene. Crystalline bexagliflozin is not hygroscopic.
Each film-coated tablet contains 20 mg of bexagliflozin and the inactive ingredients colloidal silicon dioxide, glyceryl dibehenate, lactose monohydrate, magnesium stearate, microcrystalline cellulose, polyethylene oxide, and poloxamer 188. In addition, the film coating ingredient, Opadry® II Blue 85F99153, contains the inactive ingredients FD&C Blue #1/Brilliant Blue FCF Aluminum Lake, FD&C Blue #2/Indigo Carmine Aluminum Lake, macrogol 3350, partially hydrolyzed polyvinyl alcohol, talc, and titanium dioxide.

12 CLINICAL PHARMACOLOGY

12.1 Mechanism of Action

Bexagliflozin is an inhibitor of sodium-glucose co-transporter 2 (SGLT2), the transporter responsible for reabsorption of the majority of glucose from the renal glomerular filtrate in the renal proximal tubule. By inhibiting SGLT2, bexagliflozin reduces renal reabsorption of filtered glucose and lowers the renal threshold for glucose, and thereby increases urinary glucose excretion.

12.2 Pharmacodynamics

Urinary Glucose Excretion and Urinary Volume
Dose-dependent increases in urinary glucose excretion (UGE) accompanied by increases in urine volume were observed in healthy subjects and in adults with type 2 diabetes mellitus following single- and multiple-dose administration of bexagliflozin. Dose-response analysis indicates that 20 mg bexagliflozin provides near-maximal UGE. Elevated UGE was maintained after multiple-dose administration.

Cardiac Electrophysiology
At 5 times the recommended dose, bexagliflozin does not prolong the QTc interval to any clinically significant extent.

12.3 Pharmacokinetics

The pharmacokinetics of bexagliflozin are similar in healthy subjects and adults with type 2 diabetes mellitus. Following dosing in the fasted state, mean Cmax and AUC0-∞ were 134 ng/mL and 1,162 ng·h/mL, respectively. Bexagliflozin does not exhibit time-dependent pharmacokinetics and accumulates in plasma up to ~20% following multiple dosing.

Absorption
Following oral administration of BRENZAVVY, peak plasma concentrations of bexagliflozin were reached between 2 – 4 hours post-dose and can be delayed if taken after a meal or by medications that slow gastric emptying. Plasma Cmax and AUC of bexagliflozin increase in a dose-proportional manner following single doses from 3 mg (0.15 times the recommended dose) to 90 mg (4.5 times the recommended dose).

Effect of Food
Administration of BRENZAVVY after consumption of a standard high-fat, high-caloric meal increased Cmax and AUC by 31% and 10%, respectively, compared to dosing in the fasted state. The median Tmax was increased to 5 hours. The effects of food on bexagliflozin pharmacokinetics are not considered clinically relevant [see Dosage and Administration (2.2)].

Distribution
Bexagliflozin is approximately 93% bound to plasma protein. Neither renal nor hepatic impairment substantially alters protein binding. The apparent volume of distribution is 262 L.

Elimination

Metabolism
Bexagliflozin is mainly metabolized by UGT1A9 and, to a lesser extent, CYP3A. In plasma the most abundant metabolite is the pharmacologically inactive 3′-O-glucuronide, which was found to constitute 32.2% of the parent compound AUC in a radiolabeled tracer study. None of the metabolites are expected to have clinically relevant pharmacological effects.

Excretion
The apparent oral clearance of bexagliflozin is 19.1 L/h by population pharmacokinetic modeling. The apparent terminal elimination half-life of bexagliflozin was approximately 12 hours. Following administration of an oral [^14C]-bexagliflozin solution to healthy subjects, 91.6% of input radioactivity was recovered, 51.1% in feces, the majority as bexagliflozin, and 40.5% in urine, largely as the 3′-O-glucuronide. The proportion of input radioactivity recovered as bexagliflozin in urine and feces was 1.5% and 28.7%, respectively

Specific Populations

Patients with Renal Impairment
In a clinical pharmacology study in patients with type 2 diabetes mellitus and mild (eGFR 60 to 89 mL/min/1.73 m^2), moderate (eGFR 30 to 59 mL/min/1.73 m^2), and severe (eGFR less than 30 mL/min/1.73 m^2) renal impairment, the AUC of bexagliflozin was 7%, 34% and 54% greater than in patients with normal renal function, respectively, after administration of a single 20 mg dose of BRENZAVVY. These increases in bexagliflozin AUC are not considered clinically meaningful.
Consistent with the mechanism of action of bexagliflozin, the 24-hour UGE in patients with type 2 diabetes mellitus and mild, moderate, and severe renal impairment was 17%, 60%, and 83% lower than in patients with type 2 diabetes mellitus with normal renal function, respectively. Therefore, the glucose-lowering pharmacodynamic response to bexagliflozin declines with increasing severity of renal impairment [see Dosage and Administration (2.1), Warnings and Precautions (5.3), Use in Specific Populations (8.6), and Clinical Studies (14)]. The impact of hemodialysis on bexagliflozin exposure is not known.

Patients with Hepatic Impairment
In patients with moderate hepatic impairment (Child-Pugh class B), the AUC of bexagliflozin increased by 28%, and Cmax increased by 6.3% compared to subjects with normal hepatic function. These increases in bexagliflozin AUC and Cmax are not considered clinically meaningful. There is no clinical experience in patients with Child-Pugh class C (severe) hepatic impairment [see Use in Specific Populations (8.7)

Effects of Age, Body Weight, Sex, and Race
Based on a population pharmacokinetic analysis, age, body weight, sex and race do not have a clinically relevant effect on the pharmacokinetics of bexagliflozin.

Drug Interaction Studies

In vitro Assessment of Drug Interactions
Based on in vitro studies, bexagliflozin is not expected to inhibit CYP450 isoenzymes (CYPs) 1A2, 2B6, 2C8, 2C9, 2C19, 2D6, and 3A4, or induce CYPs 1A2, 2C19 and 3A4 at clinically relevant plasma concentrations.
Bexagliflozin is not expected to inhibit drug transporters including breast cancer resistance protein (BRCP), bile salt export pump (BSEP), organic anion transporting polypeptides (OATP1B1, OATP1B3), anion transporters (OAT1, OAT3), organic cation transporters (OCT1, OCT2), and multidrug and toxin extrusion transporters (MATE1, MATE2-K) at clinically relevant plasma concentrations. Bexagliflozin is a substrate for P-glycoprotein (P-gp).

In vivo Assessment of Drug Interactions
There are no clinically meaningful changes in bexagliflozin exposure when taken with metformin, glimepiride, sitagliptin, exenatide, probenecid, or verapamil (Figure 1). Bexagliflozin had no clinically relevant effect on the pharmacokinetics of metformin, glimepiride, sitagliptin, and digoxin (Figure 2).

Figure 1. Effect of Other Drugs on the Pharmacokinetics of Bexagliflozin

Note: Rifampin dosing over 5 days, the regimen may not represent the maximal impact on bexagliflozin exposure. All others were single day dosing (once daily or twice daily).

Figure 2. Effect of Bexagliflozin on the Pharmacokinetics of Other Drugs

Note: Single day dosing.

13 NONCLINICAL TOXICOLOGY

13.1 Carcinogenesis, Mutagenesis, Impairment of Fertility

Carcinogenesis
Carcinogenesis was evaluated in 2-year studies in CD-1 mice at oral gavage doses of 15, 50, and 150 mg/kg/day and in Sprague-Dawley (SD) rats at 3, 10, and 30 mg/kg/day. In male rats, the dose was reduced to 1, 3, and 10 mg/kg/day at week 73 due to exacerbation of chronic progressive nephropathy resulting in excessive mortality. There were no drug-related neoplastic findings in mice or rats at up to the highest doses tested representing up to 156 times (mice) and 68 times (rats) the clinical dose of 20 mg based on AUC.

Mutagenesis
Bexagliflozin was not mutagenic or clastogenic with or without metabolic activation in the in vitro Ames bacterial mutagenicity assay, the in vitro CHO cell assay, an in vivo micronucleus assay in rats, and an in vivo unscheduled hepatic DNA synthesis study in rats.

Impairment of Fertility
Bexagliflozin had no effects on mating, fertility or early embryonic development in male or female rats at any dose up to the highest dose of 200 mg/kg/day, which resulted in exposures 280 times (males) and 439 times (females) the 20 mg clinical dose (based on AUC).

14 CLINICAL STUDIES

14.1 Overview of Clinical Trials

BRENZAVVY has been studied as monotherapy (Trial 1) and in combination with metformin in adults with type 2 diabetes mellitus (Trials 2, 3, and 4) [see Clinical Studies (14.2 and 14.3)]. BRENZAVVY has also been studied in adults with type 2 diabetes mellitus with moderate renal impairment (Trial 5) [see Clinical Studies (14.4)], and in adults with type 2 diabetes mellitus with established CVD or at increased risk for CVD (Trial 6) [see Clinical Studies (14.5)].
Treatment with BRENZAVVY reduced hemoglobin A1c (HbA1c) compared to placebo and efficacy was noninferior to glimepiride (up-titrated to a maximum dose of 6 mg) and sitagliptin 100 mg once daily (see Trials 3 and 4). The reduction in HbA1c by BRENZAVVY was shown across subgroups of age, sex, race, and geographic region.

14.2 Glycemic Control in Adults with Type 2 Diabetes Mellitus - Monotherapy (Trial 1)

A total of 207 adults with type 2 diabetes mellitus inadequately controlled (HbA1c between 7% and 10.5%) by diet and exercise participated in a randomized, double-blind, multi-center, 24-week, placebo-controlled trial (NCT02715258; referred to as Trial 1) to evaluate the efficacy of BRENZAVVY monotherapy. Patients were either treatment naïve or had discontinued a single oral antihyperglycemic treatment ≥ 6 weeks prior to entering a 2-week, single-blind, placebo run-in period. Upon completion of the run-in period they were randomized (1:2) to placebo or BRENZAVVY 20 mg administered orally once daily. The mean age of the population was 55 years and 4% of the patients were older than 75 years of age. Forty-eight percent (48%) were male and 74% were White, 10% were Asian, 15% were Black and 1% were other races. Fifty-two percent (52%) were Hispanic/Latino.

At week 24, treatment with BRENZAVVY provided a statistically significant reduction in HbA1c compared to placebo (see Table 5).

Table 5. Glycemic Results from a 24-Week Placebo-Controlled Monotherapy Trial of BRENZAVVY in Adults with Type 2 Diabetes Mellitus (Trial 1)

 | Placebo N = 69 | BRENZAVVY N = 138
HbA1c (%)
Baseline mean | 7.9 | 8.1
Change from baseline [adjusted mean (SE)] a | -0.1 (0.1) | -0.5 (0.1)
Difference from placebo [adjusted mean] (95% CI) | -0.4 (-0.6, -0.1)*
Proportion of patients (%) achieving HbA1c <7% b | 20% | 31%
FPG (mg/dL)
Baseline mean | 170 | 169
Change from baseline [adjusted mean (SE)] c | -3 (4) | -16 (3)
Difference from placebo [adjusted mean] (95% CI) | -14 (-24, -3)

SE: Standard Error; CI: Confidence Interval; FPG: Fasting plasma glucose
* Statistically significant (multiplicity adjusted one-sided p-value < 0.025)
a Intention to treat population. ANCOVA was used to analyze data using imputed values by return to baseline analysis for missing data at week 24 (9% and 7% for bexagliflozin and placebo, respectively). The ANCOVA model included treatment, country, background anti-diabetes treatment status (treatment naïve or not) and the baseline HbA1c value as a covariate.
b Crude proportion using imputed HbA1c values for missing data at week 24 and averaged across multiply imputed datasets
c Same model as for HbA1c endpoint but with baseline FPG instead of baseline HbA1c as a covariate.

Figure 3. Mean Change from Baseline in HbA1c (%) by Time and Treatment
Vertical lines represent 95% confidence intervals. Treatment group least squares mean changes from baseline in HbA1c were estimated by an ANCOVA model using observed data for intermediate visits. Numbers of patients per arm per measurement shown below plot. Return-to-baseline (RTB) analysis results at Week 24 are plotted to the right separately.

14.3 Glycemic Control in Adults with Type 2 Diabetes Mellitus – Combination Therapy (Trials 2, 3 and 4)

Add-on Combination Therapy with Metformin (Trial 2)
A total of 317 adults with type 2 diabetes mellitus inadequately controlled (HbA1c between 7.5% and 10.5%) by metformin monotherapy (≥ 1,000 mg/day or ≥ 1,500 mg/day for ≥ 8 weeks depending on country) participated in a randomized, double-blind, multi-center, 24-week, placebo-controlled trial (NCT03259789; referred to as Trial 2) to evaluate the efficacy of BRENZAVVY in combination with metformin. Patients entered a 1-week, single-blind, placebo run-in period, and were randomized (1:1) to placebo or BRENZAVVY 20 mg administered orally once daily in addition to the background metformin therapy. The mean age of the population was 56 years and 4% of the patients were older than 75 years of age. Sixty-one percent (61%) were male and 31% were White, 50% were Asian, 17% were Black and 2% were other races. Twenty-one percent (21%) were Hispanic/Latino.
At Week 24, treatment with BRENZAVVY provided a statistically significant reduction in HbA1c compared to placebo (see Table 6).
Table 6. Glycemic Results From a 24-Week Placebo-Controlled Trial for BRENZAVVY used in Combination with Metformin in Adults with Type 2 Diabetes Mellitus (Trial 2)

 | Placebo N = 159 | BRENZAVVY N = 158
HbA1c (%)
Baseline mean | 8.5 | 8.6
Change from baseline [adjusted mean (SE)] a | -0.5 (0.1) | -1.0 (0.1)
Difference from placebo [adjusted mean] (95% CI) | -0.5 (-0.7, -0.3)*
Proportion of patients (%) achieving HbA1c < 7% b | 10% | 26%
FPG (mg/dL)
Baseline mean | 190 | 186
Change from baseline [adjusted mean (SE)] c | -20 (3) | -42 (3)
Difference from placebo [adjusted mean] (95% CI) | -22 (-31, -12)

SE: Standard Error; CI: Confidence Interval; FPG: Fasting plasma glucose

* Statistically significant (multiplicity adjusted one-sided p-value < 0.025)
a Intention to treat population. ANCOVA was used to analyze data using imputed values by return to baseline analysis for missing data at week 24 (10% and 9% for bexagliflozin and placebo, respectively). The ANCOVA model included treatment, baseline HbA1c value and country (US or Japan).
b Crude proportion using imputed HbA1c values for missing data at week 24 and averaged across multiply imputed datasets
c Same model as for HbA1c endpoint but with baseline FPG instead of baseline HbA1c as a covariate.
Active-Controlled Trial versus Glimepiride as Add-on Therapy with Metformin (Trial 3)
A total of 426 adults with type 2 diabetes mellitus inadequately controlled (HbA1c between 7% and 10.5%) by metformin monotherapy participated in a randomized, double-blind, multi-center, 60-week, active comparator-controlled trial (NCT02769481; referred to as Trial 3) to evaluate the efficacy of BRENZAVVY in combination with metformin. Patients receiving metformin (≥ 1,500 mg/day) as monotherapy entered a 2-week, single-blind, placebo run-in period; patients receiving metformin and another oral hypoglycemic agent enrolled if they discontinued the second agent for at least 6 weeks. Upon completion of the run-in period, they were randomized (1:1) to glimepiride or BRENZAVVY 20 mg administered orally once daily in addition to the background metformin therapy. Glimepiride therapy was initiated at 2 mg/day and titrated up to 6 mg/day or the maximum tolerated dose below 6 mg/day. Glimepiride up-titration occurred until week 6 of the 60-week treatment period. The mean daily dose of glimepiride was 5.4 mg (the maximal approved dosage in the United States is 8 mg per day). Eighty-one percent of patients in the glimepiride group were titrated up to 6 mg per day. The mean age of the population was 60 years and 5% of the patients were older than 75 years of age. Fifty-eight percent (58%) were male and 94% were White, 3% were Asian, 2% were Black, and 1% were other races. Twenty-two percent (22%) were Hispanic/Latino.

Glycemic Results
BRENZAVVY was non-inferior to glimepiride in the change in HbA1c from baseline after 60 weeks of treatment (See Table 7).
Table 7. Glycemic Results from a 60-Week Active-Controlled Trial Comparing BRENZAVVY to Glimepiride as an Add-On Therapy in Adults with Type 2 Diabetes Mellitus Inadequately Controlled by Metformin (Trial 3)

 | Glimepiride N = 213 | BRENZAVVY N = 213
HbA1c (%)
Baseline mean | 8.0 | 8.0
Change from baseline [adjusted mean (SE)] a | -0.6 (0.1) | -0.7 (0.1)
Difference from glimepiride [adjusted mean] (95% CI) | -0.0 (-0.2, 0.1) b
Proportion of patients (%) achieving HbA1c < 7% c | 33% | 35%
FPG (mg/dL)
Baseline mean | 174 | 172
Change from baseline [adjusted mean (SE)] d | -14 (3) | -22 (2)
Difference from glimepiride [adjusted mean] (95% CI) | -8 (-15, -1)

SE: Standard Error; CI: Confidence Interval; FPG: Fasting plasma glucose
a Intention to treat population. ANCOVA was used to analyze data using imputed values by return to baseline analysis for missing data at week 60 (9% and 10% for bexagliflozin and glimepiride, respectively). The ANCOVA model included treatment, region, background treatment status (metformin-only or metformin + another oral hypoglycemic agent), eGFR at baseline (≥ 90 vs. < 90 mL/min/1.73 m^2), and baseline HbA1c value. Non-inferiority is declared if the upper bound of the 95% confidence interval for the difference from glimepiride lies below 0.35.
b Non-inferior
c Crude proportion using imputed HbA1c values for missing data at week 60 and averaged across multiply imputed datasets
d Same model as for HbA1c endpoint but with baseline FPG instead of baseline HbA1c as a covariate.
Body Weight and Systolic Blood Pressure Results
The mean baseline body weight in patients with baseline BMI ≥ 25 kg/m^2 was 92 kg (N = 202) and 90 kg (N = 201) in the glimepiride and BRENZAVVY groups, respectively. The mean changes from baseline to Week 60 in this population were 0.6 kg and -3.4 kg in the glimepiride and BRENZAVVY groups, respectively. The difference from glimepiride (95% CI) for BRENZAVVY was -4.0 kg (-4.8, -3.2).
The mean baseline cuff systolic blood pressure (SBP) in patients with baseline values ≥ 140 mmHg was 149 mm Hg in the glimepiride (N = 75) and BRENZAVVY (N = 78) groups. The mean changes in cuff SBP in this population from baseline to Week 60 were -6.2 mmHg and -12.9 mmHg in the glimepiride and BRENZAVVY groups, respectively. The difference from glimepiride (95% CI) for BRENZAVVY was -6.8 mmHg (-10.8, -2.6).
Active-Controlled Trial versus Sitagliptin as Add-on Therapy with Metformin (Trial 4)
A total of 384 adults with type 2 diabetes mellitus inadequately controlled (HbA1c between 7% and 11%) by metformin monotherapy participated in a randomized, double-blind, multi-center, 24-week, active comparator-controlled trial (NCT03115112; referred to as Trial 4) to evaluate the efficacy of BRENZAVVY in combination with metformin. Patients receiving metformin monotherapy (≥ 1,500 mg/day for ≥ 8 weeks) entered a 1-week, single-blind, placebo run-in period and were randomized to sitagliptin 100 mg or BRENZAVVY 20 mg administered orally once daily in addition to the background metformin therapy. The mean age of the population was 59 years and 4% of the patients were older than 75 years of age. Sixty-four percent (64%) were male and 82% were White, 16% were Asian, and 2% were Black. Three percent (3%) were Hispanic/Latino.

BRENZAVVY was non-inferior to sitagliptin in the change in HbA1c from baseline after 24 weeks of treatment.

Table 8. Glycemic Results from a 24-Week Active-Controlled Trial Comparing BRENZAVVY to Sitagliptin as an Add-On Therapy in Adults with Type 2 Diabetes Mellitus Inadequately Controlled by Metformin (Trial 4)

 | Sitagliptin N = 193 | BRENZAVVY N = 191
HbA1c (%)
Baseline mean | 8.0 | 7.9
Change from baseline [adjusted mean (SE)] a | -0.9 (0.1) | -0.8 (0.1)
Difference from sitagliptin [adjusted mean] (95% CI) | 0.1 (-0.1, 0.2)b
Proportion of patients (%) achieving HbA1c < 7% c | 45% | 40%
FPG (mg/dL)
Baseline mean | 180 | 176
Change from baseline [adjusted mean (SE)] d | -26 (2) | -31 (2)
Difference from sitagliptin [adjusted mean] (95% CI) | -5 (-11, 1)

SE: Standard Error; CI: Confidence Interval; FPG: Fasting plasma glucose
a Intention to treat population. ANCOVA was used to analyze data using imputed values by return to baseline analysis for missing data at week 24 (6% and 2% for bexagliflozin and sitagliptin, respectively). The ANCOVA model included treatment, baseline HbA1c value and region. Non-inferiority is declared if the upper bound of the 95% confidence interval for the difference from sitagliptin lies below 0.35.
b Non-inferior
c Crude proportion using imputed HbA1c values for missing data at week 24 and averaged across multiply imputed datasets
d Same model as for HbA1c endpoint but with baseline FPG instead of baseline HbA1c as a covariate.

14.4 Glycemic Control in Adults with Type 2 Diabetes Mellitus and Moderate Renal Impairment (Trial 5)

A total of 312 adults with inadequately controlled type 2 diabetes mellitus (HbA1c between 7.0% and 10.5%) and moderate renal impairment (eGFR between 30 and 60 mL/min/1.73 m^2) received BRENZAVVY or placebo in a double-blind, randomized, placebo-controlled trial (NCT02836873; referred to as Trial 5) to evaluate the efficacy of BRENZAVVY. In this trial, 77 BRENZAVVY-treated patients had an eGFR between 45 and 60 mL/min/1.73 m^2 and 74 BRENZAVVY-treated patients had an eGFR between 30 and 45 mL/min/1.73 m^2. At baseline, nearly all patients (96%) were treated with one or more antidiabetic medications including metformin (37%), insulin (58%), sulfonylureas (11%) and dipeptidyl peptidase 4 (DPP-4) inhibitors (21%). The mean age of the population was 70 years and 29% of the patients were older than 75 years of age. Sixty-three percent (63%) were male and 55% were White, 38% were Asian, 5% were Black, and 2% were other races. Eight percent (8%) were Hispanic/Latino. The mean duration of type 2 diabetes mellitus was 16 years, the mean HbA1c at baseline was 8.0% and the mean eGFR was 45 mL/min/1.73 m^2.

At week 24, treatment with BRENZAVVY provided a statistically significant reduction in HbA1c compared to placebo (Table 9).

Table 9. Glycemic Results from a 24-Week Placebo-Controlled Trial that Evaluated BRENZAVVY as a Therapy Added to Standard of Care Regimens for Adults with Type 2 Diabetes Mellitus and eGFR between 30 and 60 mL/min/1.73 m^2 (Trial 5)

 | Placebo N = 155 | BRENZAVVY N = 157
HbA1c (%)
Baseline mean | 7.9 | 8.0
Change from baseline [adjusted mean (SE)] a | -0.3 (0.1) | -0.6 (0.1)
Difference from placebo [adjusted mean] (95% CI) | -0.3 (-0.4, -0.1)*
Proportion of patients (%) achieving HbA1c < 7% b | 22% | 33%
FPG (mg/dL)
Baseline mean | 155 | 156
Change from baseline [adjusted mean (SE)] c | -8 (3) | -22 (3)
Difference from placebo [adjusted mean] (95% CI) | -14 (-23, -5)

SE: Standard Error; CI: Confidence Interval; FPG: Fasting plasma glucose

* Statistically significant (multiplicity adjusted one-sided p-value < 0.025)
a Intention to treat population. ANCOVA was used to analyze data using imputed values by return to baseline analysis for missing data at week 24 (3% and 5% for bexagliflozin and placebo, respectively). The ANCOVA model included treatment, region, screening anti-diabetic treatment regimen (insulin treated or other), baseline eGFR (< 45 or ≥ 45 mL/min/1.73m^2) and baseline HbA1c value.
b Crude proportion using imputed HbA1c values for missing data at week 24 and averaged across multiply imputed datasets
c Same model as for HbA1c endpoint but with baseline FPG instead of baseline HbA1c as a covariate.

Body Weight Results
The mean baseline body weight in patients with baseline BMI ≥ 25 kg/m^2 was 89 kg in both the placebo (N = 122) and BRENZAVVY (N = 125) groups. The mean changes from baseline to Week 24 in this population were -0.4 kg and -2.1 kg in the placebo and BRENZAVVY groups, respectively. The difference from placebo (95% CI) for BRENZAVVY was -1.7 kg (-2.4, -1.0).

14.5 Glycemic Control and Major Cardiovascular Events (MACE) in Adults with Type 2 Diabetes Mellitus and Increased Risk for Cardiovascular Disease (Trial 6)

The efficacy of BRENZAVVY was assessed in a multicenter, randomized, double-blind, placebo-controlled trial (NCT02558296; referred to as Trial 6) of adults with inadequately controlled type 2 diabetes mellitus (HbA1c between 7% and 11%) who had either established CVD (including a history of atherosclerotic vascular disease or a history of heart failure) or multiple risk factors for CVD. There were no restrictions on background antihyperglycemic medication use, aside from treatment with an SGLT2 inhibitor. After a single-blind, 2-week, placebo run-in period, 1,701 patients were randomized to receive placebo (N = 567) or BRENZAVVY 20 mg (N = 1,134) orally once daily.
At baseline, nearly all patients (99.4%) were treated with one or more antidiabetic medications including metformin (77%), insulin (53%), sulfonylureas (40%), DPP-4 inhibitors (13%) and thiazolidinediones (3%). The mean age of the population was 64 years of age and 11% of the patients were older than 75 years of age. Seventy percent (70%) were male and 77% were White, 10% were Asian, 9% were American Indian or Alaskan Native, and 4% were Black. Fifteen percent (15%) were Hispanic/Latino. At baseline, the mean duration of diabetes was 15 years and the mean HbA1c was 8.3%. The mean baseline eGFR was 78 mL/min/1.73 m^2; 80% of patients had an eGFR > 60 mL/min/1.73 m^2 and 20% of patients had an eGFR 45 to 60 mL/min/1.73 m^2.
Glycemic Response
Treatment with BRENZAVVY provided a statistically significant reduction in HbA1c at Week 24 compared to treatment with placebo (see Table 10). In addition, BRENZAVVY provided a statistically significant reduction in HbA1c compared to placebo in a subset of patients using background insulin (N = 902, difference from placebo -0.5% [95% CI: -0.6, -0.4]) and in a subset of patients using background sulfonylureas (N = 313, difference from placebo -0.4% [95% CI:-0.6, -0.2]).

Table 10. Glycemic Results from a 24-Week Trial in Adults with Type 2 Diabetes Mellitus with Established CVD or Multiple CVD Risk Factors (Trial 6)

 | Placebo N = 567 | BRENZAVVY N = 1133
HbA1c (%)
Baseline mean | 8.3 | 8.3
Change from baseline [adjusted mean (SE)] a | -0.4 (0.04) | -0.8 (0.03)
Difference from placebo [adjusted mean] (95% CI) | -0.4 (-0.5, -0.4)*
Proportion of patients (%) achieving HbA1c < 7% b | 17% | 29%
FPG (mg/dL)
Baseline mean | 162 | 166
Change from baseline [adjusted mean (SE)] c | -4 (2) | -23 (1)
Difference from placebo [adjusted mean] (95% CI) | -20 (-24, -15)

SE: Standard Error; CI: Confidence Interval; FPG: Fasting plasma glucose
* Statistically significant (multiplicity adjusted one-sided p-value < 0.025)
a Intention to treat population. ANCOVA was used to analyze data using imputed values by return to baseline analysis for missing data at week 24 (7% and 6% for bexagliflozin and placebo, respectively). The ANCOVA model included treatment, region, baseline eGFR category (< 60 or ≥ 60 mL/min/1.73m^2), baseline BMI category (< 25 or ≥ 25 kg/m^2), history of heart failure (yes or no), insulin use or not, and baseline HbA1c value.
b Crude proportion using imputed HbA1c values for missing data at week 24 and averaged across multiply imputed datasets
c Same model as for HbA1c endpoint but with baseline FPG instead of baseline HbA1c as a covariate.

Body Weight and Systolic Blood Pressure Results
The mean baseline body weight in a subgroup of patients with baseline BMI ≥ 25 kg/m^2 was 95 kg (N = 522) and 97 kg (N = 1047) in the placebo and BRENZAVVY groups, respectively. The mean changes from baseline to Week 24 were -0.3 kg and -2.7 kg in the placebo and BRENZAVVY groups, respectively. The difference from placebo (95% CI) for BRENZAVVY was -2.3 kg (-2.8, -1.9).

The mean baseline systolic blood pressure (SBP) in a subgroup of patients with baseline values ≥ 140 mmHg was 150 mmHg in the placebo (N = 215) and BRENZAVVY (N = 448) groups. The mean changes in SBP from baseline to Week 24 were -6.6 mmHg and -9.2 mmHg in the placebo and BRENZAVVY groups, respectively. The difference from placebo (95% CI) for BRENZAVVY was -2.7 mmHg (-5.2, -0.1).

Major Adverse Cardiovascular Events (MACE) Results
Trial 6 was used to assess the impact of BRENZAVVY on MACE (a composite of cardiovascular death, non-fatal myocardial infarction, nonfatal stroke, and hospitalization for unstable angina). The minimum treatment duration was 52 weeks (median duration 2.4 years). In this trial, the proportion of patients who experienced at least one MACE event was 10.1% (57/567) in the placebo group and 7.9% (89/1132) in the BRENZAVVY group (4.2 MACE events per 100 person-years for placebo and 3.3 MACE events per 100 person-years for BRENZAVVY). No increased risk for MACE was observed in the BRENZAVVY group compared to the control group [estimated hazard ratio of 0.77 (95% CI: 0.56, 1.08)]. The BRENZAVVY group was not superior to the placebo group in reducing MACE.

16 HOW SUPPLIED/STORAGE AND HANDLING

BRENZAVVY 20 mg tablets are blue, caplet-shaped, biconvex, bevel-edged, film-coated debossed with “2” and inverted “2” on one side.
• Bottles of 30 tablets – NDC 82381-2174-1
• Bottles of 90 tablets – NDC 82381-2174-2
Storage and Handling
Store from 20 °C to 25 °C (68 °F to 77 °F); excursions permitted between 15 °C to 30 °C (59 °F to 86 °F) [see USP Controlled Room Temperature].

17 PATIENT COUNSELING INFORMATION

Advise the patient to read the FDA-approved patient labeling (Medication Guide).
Diabetic Ketoacidosis in Patients with Type 1 Diabetes Mellitus and Other Ketoacidosis
Inform patients that BRENZAVVY can cause potentially fatal ketoacidosis and that type 2 diabetes mellitus and pancreatic disorders (e.g., history of pancreatitis or pancreatic surgery) are risk factors.
Educate all patients on precipitating factors (such as insulin dose reduction or missed insulin doses, infection, reduced caloric intake, ketogenic diet, surgery, dehydration, and alcohol abuse) and symptoms of ketoacidosis (including nausea, vomiting, abdominal pain, tiredness, and labored breathing). Inform patients that blood glucose may be normal even in the presence of ketoacidosis.
Advise patients that they may be asked to monitor ketones. If symptoms of ketoacidosis occur, instruct patients to discontinue BRENZAVVY and seek medical attention immediately [see Warnings and Precautions (5.1)].

Lower Limb Amputation
Inform patients of the potential for an increased risk of amputations with BRENZAVVY. Counsel patients on the importance of routine preventive foot care. Instruct patients to monitor for any new pain or tenderness, sores or ulcers, or infections involving the leg or foot and to seek medical advice immediately if such signs or symptoms develop [see Warnings and Precautions (5.2)].

Volume Depletion
Inform patients that symptomatic hypotension may occur with BRENZAVVY and advise them to contact their healthcare provider if they experience such symptoms. Inform patients that dehydration may increase the risk of hypotension, and to maintain adequate fluid intake. [see Warnings and Precautions (5.3)].

Genitourinary Infections, including Urosepsis, Pyelonephritis, Necrotizing Fasciitis of the Perineum (Fournier’s Gangrene), and Genital Mycotic Infections
Counsel patients that genitourinary infections may occur when taking BRENZAVVY and may become serious. Educate them on the symptoms and advise them to seek medical advice if symptoms occur. Specifically, advise patients to promptly seek medical attention if they develop pain or tenderness, redness, or swelling of the genitals or the area from the genitals back to the rectum, along with a fever above 100.4°F or malaise. [see Warnings and Precautions (5.4)].

Hypoglycemia with Concomitant Use with Insulin and Insulin Secretagogues
Inform patients that the incidence of hypoglycemia may increase when BRENZAVVY is added to insulin and/or an insulin secretagogue. Educate patients or caregivers on the signs and symptoms of hypoglycemia [see Warnings and Precautions (5.5)].

Pregnancy
Advise pregnant patients and females of reproductive potential of the potential risk to a fetus with treatment with BRENZAVVY. Instruct patients to inform their healthcare provider if pregnant or planning to become pregnant [see Use in Specific Populations (8.1)].

Lactation
Advise patients that breastfeeding is not recommended during treatment with BRENZAVVY [see Use in Specific Populations (8.2)].

Laboratory Tests
Inform patients that their urine will test positive for glucose while taking BRENZAVVY due to its mechanism of action. [see Drug Interactions (7)]

Missed Dose
Instruct patients to take BRENZAVVY only as prescribed. If a dose is missed, it should be taken as soon as possible. Advise patients not to double their next dose.

Distributed by:
TheracosBio, LLC
945 Concord Street
Framingham, MA 01701 USA
BRENZAVVY is a registered trademark of TheracosBio, LLC
Other brands listed are the trademarks of their respective owners and are not trademarks of TheracosBio, LLC
Copyright © 2025 TheracosBio, LLC
All rights reserved.

MEDGUIDE SECTION

MEDICATION GUIDE
BRENZAVVY® (bren-ZA-vee)
(bexagliflozin) tablets
for oral use

What is the most important information I should know about BRENZAVVY?
BRENZAVVY can cause serious side effects, including:

- Diabetic Ketoacidosis (increased ketones in your blood or urine) in people with type 1 diabetes and other ketoacidosis. BRENZAVVY can cause ketoacidosis that can be life-threatening and may lead to death. Ketoacidosis is a serious condition which needs to be treated in a hospital. People with type 1 diabetes have a high risk of getting ketoacidosis. People with type 2 diabetes or pancreas problems also have an increased risk of getting ketoacidosis. Ketoacidosis can also happen in people who: are sick, cannot eat or drink as usual, skip meals, are on a diet high in fat and low in carbohydrates (ketogenic diet), take less than the usual amount of insulin or miss insulin doses, drink too much alcohol, have a loss of too much fluid from the body (volume depletion), or who have surgery. Ketoacidosis can happen even if your blood sugar is less than 250 mg/dL. Your healthcare provider may ask you to periodically check ketones in your urine or blood.
  Stop taking BRENZAVVY and call your healthcare provider or get medical help right away if you get any of the following. If possible, check for ketones in your urine or blood, even if your blood sugar is less than 250 mg/dL.
  o nausea o tiredness
  o vomiting o trouble breathing
  o stomach-area (abdominal) pain o ketones in your urine or blood
- Amputations. BRENZAVVY may increase your risk of lower limb amputations. Amputations mainly involve removal of the toe or part of the foot, however, amputations involving the leg, below and above the knee, have also occurred. Some people had more than one amputation.
  You may be at a higher risk of lower limb amputation if you:
  - have a history of amputation
  - have heart disease or are at risk for heart disease
  - have had blocked or narrowed blood vessels, usually in your leg
  - have damage to the nerves (neuropathy) in your leg
  - have had diabetic foot ulcers or sores
  Call your healthcare provider right away if you have new pain or tenderness, any sores, ulcers, or infections in your leg or foot. Your healthcare provider may decide to stop your BRENZAVVY for a while if you have these signs or symptoms. Talk to your healthcare provider about proper foot care.
- Dehydration. BRENZAVVY can cause some people to become dehydrated (the loss of body water and salt). Dehydration can make you feel dizzy, faint, light-headed, or weak, especially when you stand up (orthostatic hypotension). There have been reports of sudden worsening of kidney function in people who are taking BRENZAVVY.
  You may be at higher risk of dehydration if you:
  - take medicines that lower your blood pressure, including diuretics (water pills)
  - are on a low sodium (salt) diet
  - have kidney problems
  - are 65 years of age or older
  Talk to your healthcare provider about what you can do to prevent dehydration including how much fluid you should drink on a daily basis. Call your healthcare provider right away if you reduce the amount of food or liquid you drink, for example if you are sick or cannot eat, or start to lose liquids from your body, for example from vomiting or diarrhea.
- Genital and urinary tract infections. BRENZAVVY can cause serious infections in your genital area or urinary tract that could require hospitalization. A rare but serious bacterial infection called necrotizing fasciitis can cause damage to the tissue under the skin in the area between and around the anus and genitals (perineum). This infection may require hospitalization, multiple surgeries, and could lead to death. Seek medical attention immediately if you have a fever or you are feeling very weak, tired or uncomfortable (malaise), and you develop any of the following symptoms in the area between and around your anus and genitals:

o pain or tenderness o swelling o redness of skin (erythema)
Also tell your healthcare provider if you have any of these signs or symptoms of urinary tract infections or yeast infections:

- Urinary tract infection:
  • burning feeling when you urinate
  • need to urinate often or right away
  • pain in the lower part of your stomach (pelvis)
  • blood in your urine
  You may also have a fever, back pain, nausea or vomiting

- Vaginal yeast infection:
  • vaginal odor
  • white or yellowish vaginal discharge (may be lumpy or look like cottage cheese)
  • vaginal itching

- Yeast infection of the skin around the penis (balanitis or balanoposthitis); If you are uncircumcised, swelling may make it difficult to pull back the skin around the tip of your penis. Other symptoms include:
  • redness, itching, or swelling of the penis • rash on the penis
  • bad smelling discharge from the penis • pain in the skin around the penis
  Talk to your healthcare provider about what to do if you get symptoms of a yeast infection. They may suggest you use an over-the-counter antifungal medicine. Contact your healthcare provider right away if your symptoms do not improve using an over-the-counter antifungal medicine

What is BRENZAVVY?

- BRENZAVVY is a prescription medicine used along with diet and exercise to improve blood sugar (glucose) in adults with type 2 diabetes.
- BRENZAVVY is not recommended to decrease blood sugar in people with type 1 diabetes.
- It is not known if BRENZAVVY is safe and effective in children under 18 years of age.

Do not take BRENZAVVY if you:

- are allergic to bexagliflozin or any of the ingredients in BRENZAVVY. See the end of this Medication Guide for a list of ingredients in BRENZAVVY. Symptoms of a serious allergic reaction to BRENZAVVY may include:
  o skin rash
  o raised red patches on your skin (hives)
  o swelling of the face, lips, tongue, and throat that may cause difficulty in breathing or swallowing

Before you take BRENZAVVY, tell your healthcare provider about all of your medical conditions, including if you:

- have type 1 diabetes or have had diabetic ketoacidosis
- have a decrease in your insulin dose
- have a serious infection
- have a history of infection of the vagina or penis
- have a history of amputation
- have had blocked or narrowed blood vessels, usually in your leg
- have damage to the nerves (neuropathy) in your leg
- have had diabetic foot ulcers or sores
- have kidney problems
- have liver problems
- have a history of urinary tract infections or problems with urination
- have or have had problems with your pancreas, including pancreatitis or surgery on your pancreas
- are on a low sodium (salt) diet. Your healthcare provider may change your diet or your dose.
- are going to have surgery. Your healthcare provider may stop your BRENZAVVY before you have surgery. Talk to your healthcare provider if you are having surgery about when to stop taking BRENZAVVY and when to start it again.
- are eating less or there is a change in your diet
- are dehydrated
- drink alcohol very often or drink a lot of alcohol in the short term (“binge” drinking).
- have ever had an allergic reaction to BRENZAVVY
- are pregnant or planning to become pregnant. BRENZAVVY may harm your unborn baby. If you become pregnant while taking BRENZAVVY, tell your healthcare provider as soon as possible. Talk with your healthcare provider about the best way to control your blood sugar while you are pregnant.
- are breastfeeding or plan to breastfeed. BRENZAVVY may pass into your breast milk and may harm your baby. Talk with your healthcare provider about the best way to feed your baby if you take BRENZAVVY. Do not breastfeed while taking BRENZAVVY.

Tell your healthcare provider about all the medicines you take, including prescription and over-the-counter medicines, vitamins, and herbal supplements.
BRENZAVVY may affect the way other medicines work, and other medicines may affect how BRENZAVVY works.
Know the medicines you take. Keep a list of them to show your healthcare provider and pharmacist when you get a new medicine.

How should I take BRENZAVVY?

- Take BRENZAVVY exactly as your healthcare provider tells you to take it.
- Take BRENZAVVY by mouth 1 time in the morning, with or without food.
- Do not crush or chew BRENZAVVY tablets.
- Your healthcare provider may tell you to take BRENZAVVY along with other diabetes medicines. Low blood sugar can happen more often when BRENZAVVY is taken with certain other diabetes medicines. See “What are the possible side effects of BRENZAVVY?”
- If you miss a dose, take it as soon as you remember. If it is time for your next dose, skip the missed dose and take the medicine at the next regularly scheduled time. Do not take 2 doses of BRENZAVVY at the same time. Talk with your healthcare provider if you have questions about a missed dose.
- If you take too much BRENZAVVY, call your healthcare provider or go to the nearest hospital emergency room right away.
- When your body is under some types of stress, such as fever, trauma (such as a car accident), infection, fasting, binge drinking or surgery, the amount of diabetes medicine that you need may change. Tell your healthcare provider as soon as possible if you have any of these conditions and follow your healthcare provider’s instructions.
- BRENZAVVY will cause your urine to test positive for glucose.
- Your healthcare provider may do certain blood tests before you start BRENZAVVY and during treatment as needed. Your healthcare provider may change your dose of BRENZAVVY based on the results of your blood tests.

What are the possible side effects of BRENZAVVY?
BRENZAVVY may cause serious side effects, including:

- See “What is the most important information I should know about BRENZAVVY?”
- serious urinary tract infections. Serious urinary tract infections that may lead to hospitalization have happened in people who are taking BRENZAVVY. Tell your healthcare provider if you have signs or symptoms of a urinary tract infection such as a burning feeling when passing urine, a need to urinate often, the need to urinate right away, pain in the lower part of your stomach (pelvis), or blood in the urine. Sometimes people also may have a fever, back pain, nausea or vomiting.
- low blood sugar (hypoglycemia). If you take BRENZAVVY with another medicine that can cause low blood sugar such as a sulfonylurea or insulin, your risk of getting low blood sugar is higher. The dose of your sulfonylurea or insulin may need to be lowered while you take BRENZAVVY. Signs or symptoms of low blood sugar may include:
  o headache o drowsines o sweating
  o confusion o dizziness o irritability
  o hunger o fast heartbeat
  o shaking or feeling jittery o weakness

- a rare but serious bacterial infection that causes damage to the tissue under the skin (necrotizing fasciitis) in the area between and around the anus and genitals (perineum). Necrotizing fasciitis of the perineum has happened in people who take BRENZAVVY. Necrotizing fasciitis of the perineum may lead to hospitalization, may require multiple surgeries, and may lead to death. Seek medical attention immediately if you have fever or you are feeling very weak, tired or uncomfortable (malaise) and you develop any of the following symptoms in the area between and around your anus and genitals:
  o pain or tenderness o swelling o redness of the skin (eyrthema)

- Serious allergic reaction. If you have any symptoms of a serious allergic reaction, stop taking BRENZAVVY and call your healthcare provider right away or go to the nearest hospital emergency room. See “Do not take BRENZAVVY if you:”. Your healthcare provider may give you a medicine for your allergic reaction and prescribe a different medicine for your diabetes.

The most common side effect of BRENZAVVY include:

- vaginal yeast infections
- urinary tract infections
- changes in urination, including urgent need to urinate more often, in larger amounts, or at night.

These are not all the possible side effects of BRENZAVVY. For more information, ask your healthcare provider or pharmacist.
Call your doctor for medical advice about side effects. You may report side effects to FDA at 1-800-FDA-1088.

How should I store BRENZAVVY?
Store BRENZAVVY at room temperature between 68 °F to 77 °F (20 °C to 25 °C).
Keep BRENZAVVY and all medicines out of the reach of children.

General information about the safe and effective use of BRENZAVVY.
Medicines are sometimes prescribed for purposes other than those listed in a Medication Guide. Do not use BRENZAVVY for a condition for which it was not prescribed. Do not give BRENZAVVY to other people, even if they have the same symptoms you have. It may harm them. You can ask your pharmacist or healthcare provider for information about BRENZAVVY that is written for health professionals.

What are the ingredients in BRENZAVVY?
Active ingredient: bexagliflozin
Inactive ingredients: colloidal silicon dioxide, glyceryl dibehenate, lactose monohydrate, magnesium stearate, microcrystalline cellulose, polyethylene oxide, and poloxamer 188. In addition, the film coating ingredient, Opadry® II Blue 85F99153, contains the inactive ingredients FD&C Blue #1/Brilliant Blue FCF and FD&C Blue #2/Indigo Carmine, macrogol 3350, polyvinyl alcohol, talc, and titanium dioxide.
Distributed by:
TheracosBio, LLC
945 Concord Street
Framingham, MA 01701 USA
BRENZAVVY is a registered trademark of TheracosBio, LLC
Other brands listed are the trademarks of their respective owners and are not trademarks of TheracosBio, LLC
Copyright © 2025 TheracosBio, LLC
ALL RIGHTS RESERVED
For more information about BRENZAVVY, go to www.brenzavvy.com or call 1-855-BRENZAVVY (1-855-273-6928).

This Medication Guide has been approved by the U.S. Food and Drug Administration Issued: 11/2025